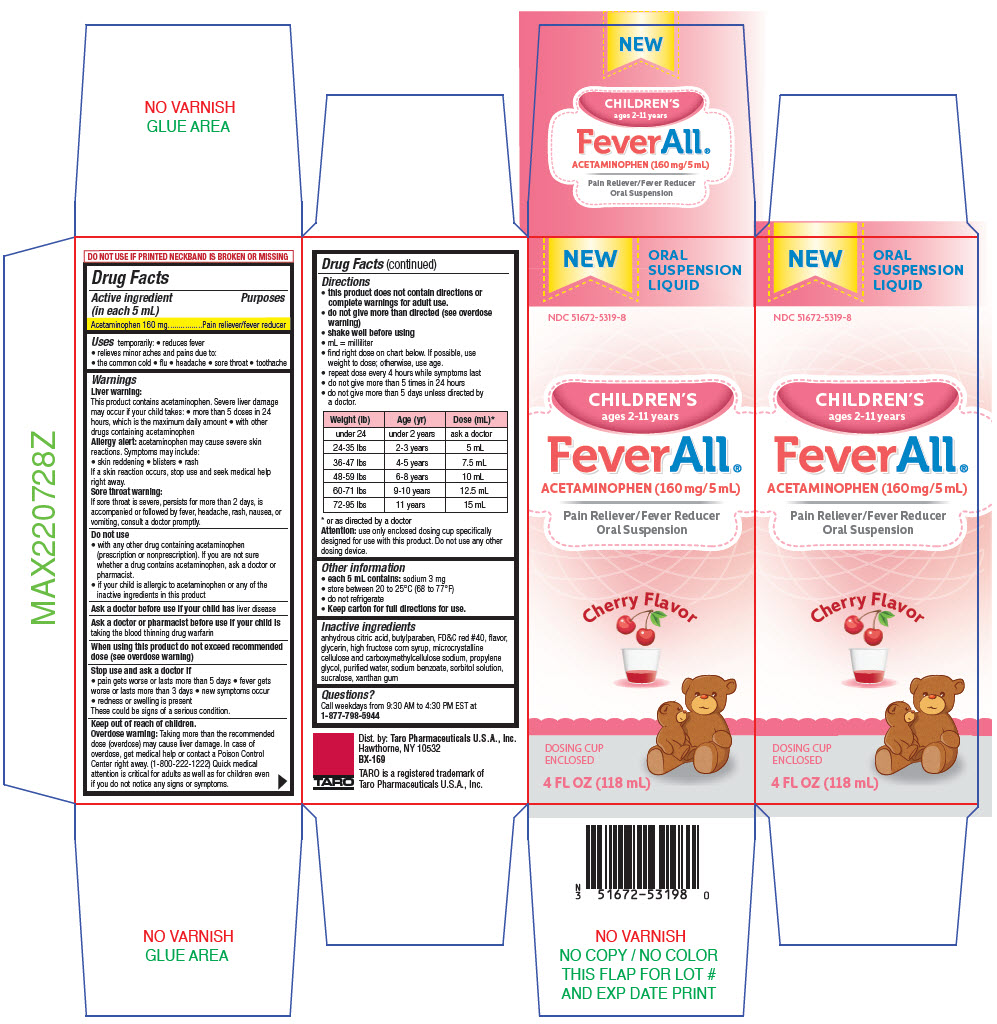 DRUG LABEL: FeverAll
NDC: 51672-5319 | Form: SUSPENSION
Manufacturer: Sun Pharmaceutical Industries, Inc.
Category: otc | Type: HUMAN OTC DRUG LABEL
Date: 20250702

ACTIVE INGREDIENTS: ACETAMINOPHEN 160 mg/5 mL
INACTIVE INGREDIENTS: ANHYDROUS CITRIC ACID; BUTYLPARABEN; FD&C RED NO. 40; GLYCERIN; HIGH FRUCTOSE CORN SYRUP; MICROCRYSTALLINE CELLULOSE; CARBOXYMETHYLCELLULOSE SODIUM, UNSPECIFIED; PROPYLENE GLYCOL; WATER; SODIUM BENZOATE; SORBITOL SOLUTION; SUCRALOSE; XANTHAN GUM

FeverAll®

Drug Facts

Active ingredient (in each 5 mL)

Acetaminophen 160 mg

Purposes

Pain reliever/fever reducer

Uses

temporarily:

- reduces fever
- relieves minor aches and pains due to:
  - the common cold
  - flu
  - headache
  - sore throat
  - toothache

Warnings

Liver warning

This product contains acetaminophen. Severe liver damage may occur if your child takes:

- more than 5 doses in 24 hours, which is the maximum daily amount
- with other drugs containing acetaminophen

Allergy alert:acetaminophen may cause severe skin reactions. Symptoms may include:

- skin reddening
- blisters
- rash

If a skin reaction occurs, stop use and seek medical help right away.

Sore throat warning

If sore throat is severe, persists for more than 2 days, is accompanied or followed by fever, headache, rash, nausea, or vomiting, consult a doctor promptly.

Do not use

- with any other drug containing acetaminophen (prescription or nonprescription). If you are not sure whether a drug contains acetaminophen, ask a doctor or pharmacist.
- if your child is allergic to acetaminophen or any of the inactive ingredients in this product

Ask a doctor before use if your child hasliver disease

Ask a doctor or pharmacist before use if your child istaking the blood thinning drug warfarin

When using this product do not exceed recommended dose (see overdose warning)

Stop use and ask a doctor if

- pain gets worse or lasts more than 5 days
- fever gets worse or lasts more than 3 days
- new symptoms occur
- redness or swelling is present

These could be signs of a serious condition.

Keep out of reach of children.

Overdose warning

Taking more than the recommended dose (overdose) may cause liver damage. In case of overdose, get medical help or contact a Poison Control Center right away. (1-800-222-1222) Quick medical attention is critical for adults as well as for children even if you do not notice any signs or symptoms.

Directions

- this product does not contain directions or complete warnings for adult use.
- do not give more than directed (see overdose warning)
- shake well before using
- mL = milliliter
- find right dose on chart below. If possible, use weight to dose; otherwise, use age.
- repeat dose every 4 hours while symptoms last
- do not give more than 5 times in 24 hours
- do not give more than 5 days unless directed by a doctor.

Weight (lb) | Age (yr) | Dose (mL) [or as directed by a doctor]
under 24 | under 2 years | ask a doctor
24-35 lbs | 2-3 years | 5 mL
36-47 lbs | 4-5 years | 7.5 mL
48-59 lbs | 6-8 years | 10 mL
60-71 lbs | 9-10 years | 12.5 mL
72-95 lbs | 11 years | 15 mL

Attention:use only enclosed dosing cup specifically designed for use with this product. Do not use any other dosing device.

Other information

- each 5 mL contains:sodium 3 mg
- store between 20 to 25°C (68 to 77°F)
- do not refrigerate
- Keep carton for full directions for use.

Inactive ingredients

anhydrous citric acid, butylparaben, FD&C red #40, flavor, glycerin, high fructose corn syrup, microcrystalline cellulose and carboxymethylcellulose sodium, propylene glycol, purified water, sodium benzoate, sorbitol solution, sucralose, xanthan gum

Questions?

Call weekdays from 9:30 AM to 4:30 PM EST at 1-877-798-5944

Dist. by: Taro Pharmaceuticals U.S.A., Inc.
Hawthorne, NY 10532

PRINCIPAL DISPLAY PANEL - 118 mL Bottle Carton

NEW

ORAL
SUSPENSION
LIQUID

NDC 51672-5319-8

CHILDREN'S
ages 2-11 years

FeverAll®
ACETAMINOPHEN (160 mg/5 mL)

Pain Reliever/Fever Reducer
Oral Suspension

Cherry Flavor

DOSING CUP
ENCLOSED

4 FL OZ (118 mL)